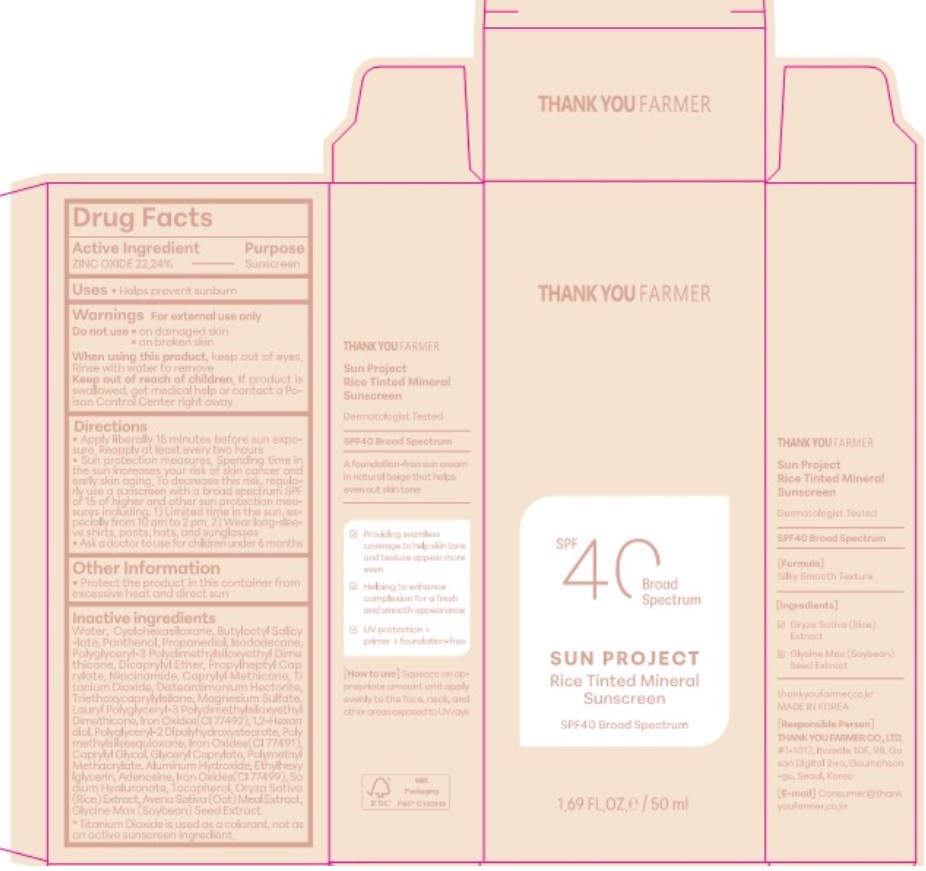 DRUG LABEL: THANK YOU FARMER Sun Project Rice Tinted Mineral Sun Cream
NDC: 70618-050 | Form: CREAM
Manufacturer: THANK YOU FARMER CO., LTD
Category: otc | Type: HUMAN OTC DRUG LABEL
Date: 20260114

ACTIVE INGREDIENTS: ZINC OXIDE 11.12 g/50 mL
INACTIVE INGREDIENTS: ETHYLHEXYLGLYCERIN; CAPRYLYL GLYCOL; OATMEAL; ISODODECANE; 1,2-HEXANEDIOL; NIACINAMIDE; DISTEARDIMONIUM HECTORITE; CYCLOMETHICONE 6; CAPRYLYL TRISILOXANE; TRIETHOXYCAPRYLYLSILANE; ADENOSINE; MAGNESIUM SULFATE ANHYDROUS; PROPANEDIOL; DICAPRYLYL ETHER; BUTYLOCTYL SALICYLATE; PROPYLHEPTYL CAPRYLATE; RICE GERM; ALUMINUM HYDROXIDE; POLYMETHYLSILSESQUIOXANE (11 MICRONS); POLY(METHYL METHACRYLATE; 450000 MW); PANTHENOL; GLYCERYL CAPRYLATE; HYALURONATE SODIUM; WATER; TITANIUM DIOXIDE; POLYGLYCERYL-2 DIPOLYHYDROXYSTEARATE; SOYBEAN; TOCOPHEROL; FERRIC OXIDE RED; POLYGLYCERYL-3 POLYDIMETHYLSILOXYETHYL DIMETHICONE (4000 MPA.S); FERRIC OXIDE YELLOW

Active Ingredient

Active Ingredient-ZINC OXIDE 22.24%

Purpose

Purpose-Sunscreen, Uses-Helps prevent sunburn

When using

When using this product, keep out of eyes. Rinse with water to remove

Keep Out Of Reach of Children- If product is swallowed, get medical help or contact a Poison Control Center right away

Ask a doctor to use for children under 6 months

Do not use on damaged skin, on broken skin

Warning

For external use only

Inactive Ingredients

WATER, CYCLOHEXASILOXANE, BUTYLOCTYL SALICYLATE, PANTHENOL, PROPANEDIOL, ISODODECANE, POLYGLYCERYL-3 POLYDIMETHYLSILOXYETHYL DIMETHICONE, DICAPRYLYL ETHER, PROPYLHEPTYL CAPRYLATE, NIACINAMIDE, CAPRYLYL METHICONE ,TITANIUM DIOXIDE, DISTEARDIMONIUM HECTORITE, TRIETHOXYCAPRYLYLSILANE, MAGNESIUM SULFATE, LAURYL POLYGLYCERYL-3 POLYDIMETHYLSILOXYETHYL DIMETHICONE, IRON OXIDES(CI 77492), 1,2-HEXANEDIOL, POLYGLYCERYL-2 DIPOLYHYDROXYSTEARATE ,POLYMETHYLSILSESQUIOXANE, IRON OXIDES(CI 77491), CAPRYLYL GLYCOL, GLYCERYL CAPRYLATE, POLYMETHYL METHACRYLATE, ALUMINUM HYDROXIDE, ETHYLHEXYLGLYCERIN, ADENOSINE, IRON OXIDES(CI 77499), SODIUM HYALURONATE, TOCOPHEROL ORYZA SATIVA (RICE) EXTRACT, AVENA SATIVA (OAT) MEAL EXTRACT, GLYCINE MAX (SOYBEAN) SEED EXTRACT

Other Safety Information-Protect the product in this container from excessive heat and direct sun

Incations & usage

Incations & usage-Helps prevent sunburn

Dosage & administration

Dosage & administration -Apply liberally 15 minutes before sun exposure. Reapply at least every two hours

Package Label Principal Display Panel-Thank you Farmer, SPF40 Broad Spectrum, Sun Project Rice Tinted Mineral Sinscren, SPF40 Broad Spectrum, 1.69 FL.OZ/50ml